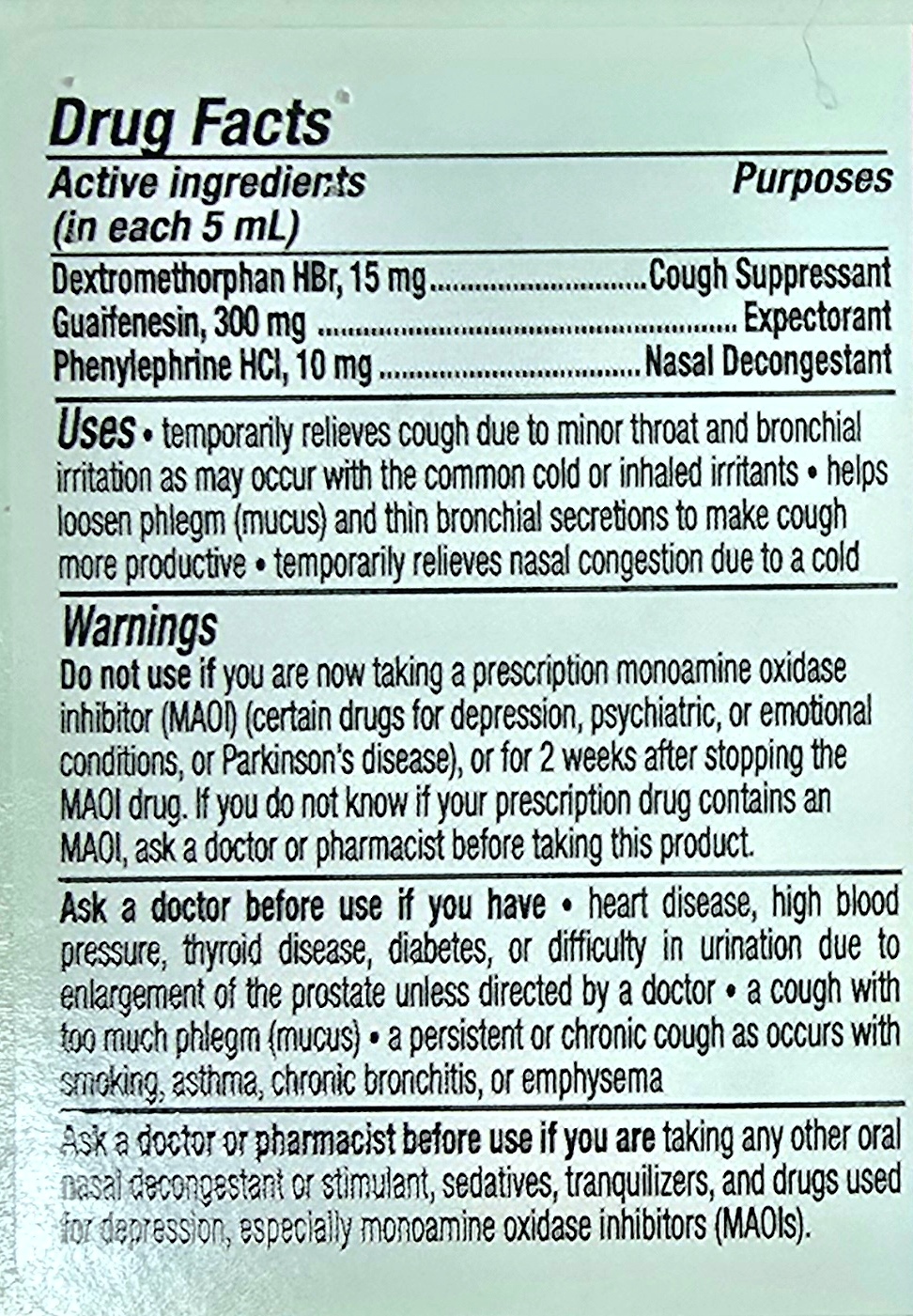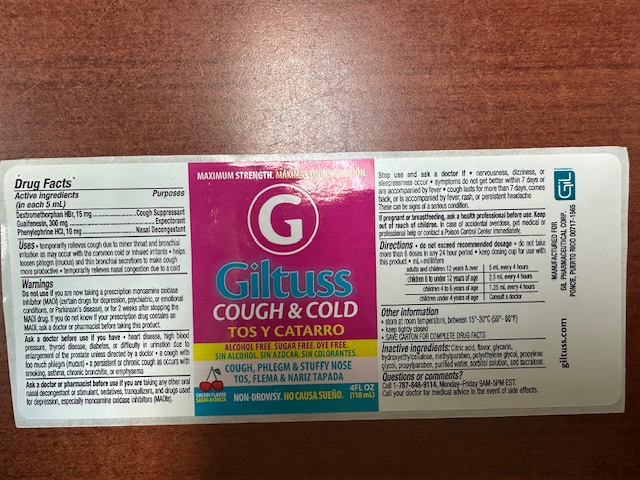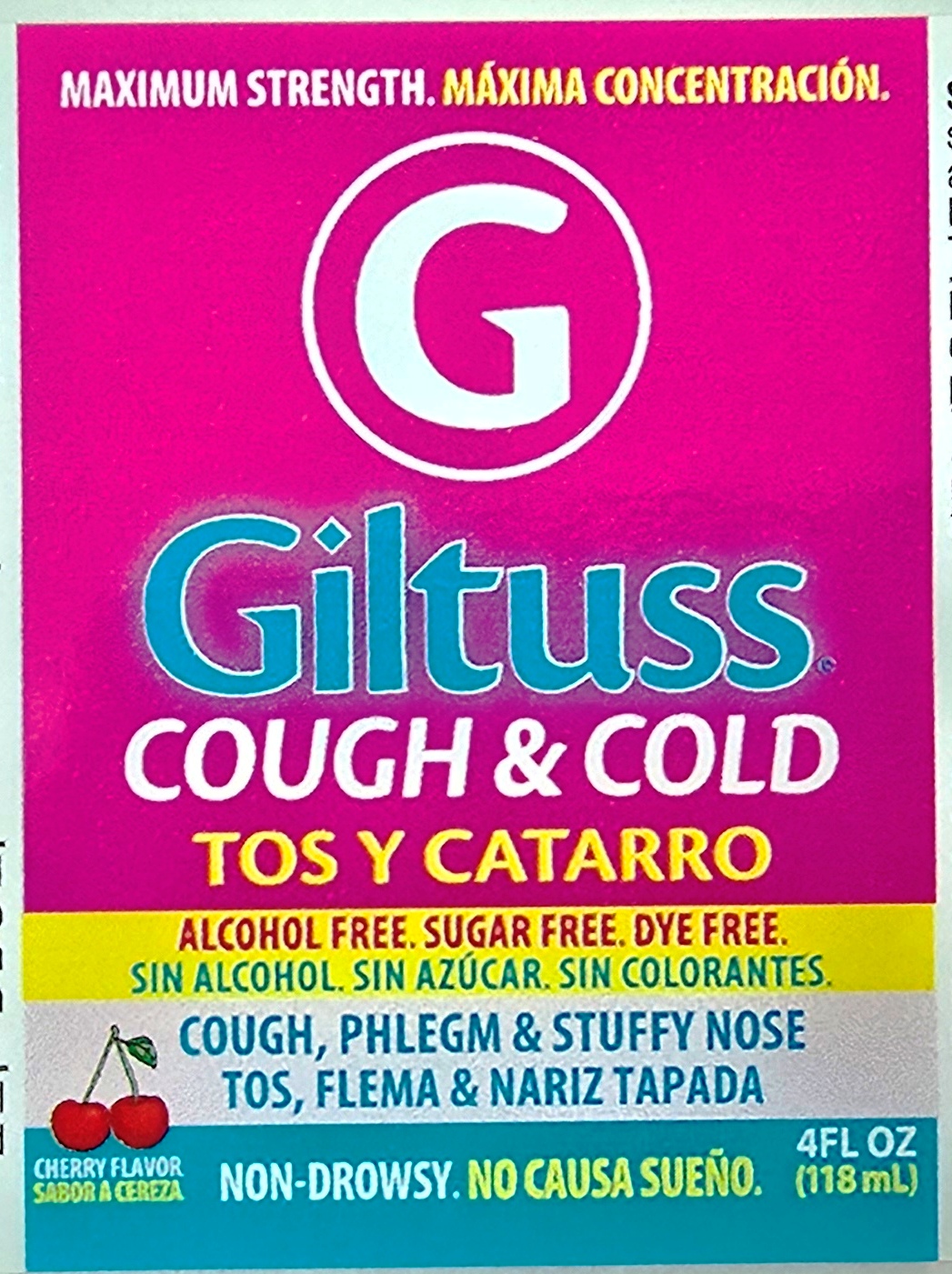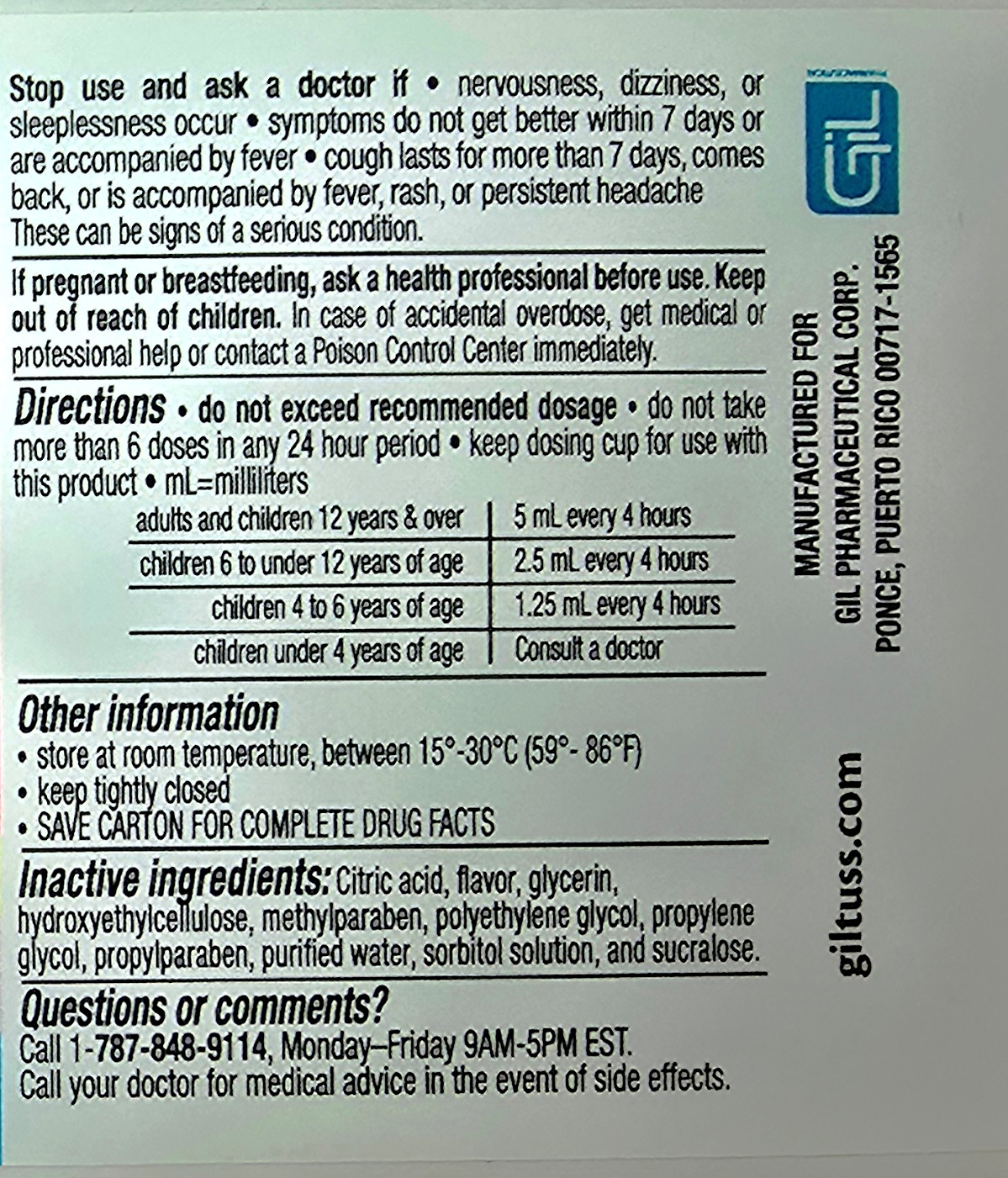 DRUG LABEL: Giltuss Cough and Cold
NDC: 65852-012 | Form: SOLUTION
Manufacturer: Dextrum Laboratories Inc.
Category: otc | Type: HUMAN OTC DRUG LABEL
Date: 20250918

ACTIVE INGREDIENTS: DEXTROMETHORPHAN HYDROBROMIDE 15 mg/5 mL; PHENYLEPHRINE HYDROCHLORIDE 10 mg/5 mL; GUAIFENESIN 300 mg/5 mL
INACTIVE INGREDIENTS: PROPYLENE GLYCOL; HYDROXYETHYLCELLULOSE; SORBITOL SOLUTION; CITRIC ACID; SUCRALOSE; METHYLPARABEN; WATER; GLYCERIN; POLYETHYLENE GLYCOL, UNSPECIFIED; PROPYLPARABEN

Giltuss Cough and Cold

Active Ingredients (in each 5 mL)

Dextromethorphan HBr , 15 mg

Guaifenesin, 300 mg

Phenylephryne HCl, 10 mg

Purpouse Section & Uses

Cough supressant

Expectorant

Nasal Descongestant

Uses

temporary relieves cough due to minor throat and bronchial irritations as may occur with the common cold or inhaled irritants, helps loosen phlegm (mucus) and thin bronchial secretions to make cough more productive, temporary relieves nasal congestion due to a cold.

Warnings

Do not use if you are now taking a prescription monoamine oxidase inhibitor (MAOI)(certain drugs for depression, psychiatric, or emotional conditions, or Parkinson's disease), or for 2 weeks after stopping the MAOI drug. If you dont know if your prescription drug contains and MAOI , ask a doctor or pharmacist before taking this product,

Ask a doctor before use if you have, heart disease, high blood pressure, thryroid disease, diabetes, or difficulty in urination due to enlargement of the prostate unless directed by a doctor, cough with too much phlegm (mucus), a persistent or chronic cough as occurs with smoking, asthma,chronic bronchitis, or ephysema

Ask a doctor or pharmacist

Ask a doctor o pharmacist before use if you are taking any other oral nasal decongestant or stimulant, sedatives , tranquilizer, and drugs used for depression, especially monoamine oxidase inhibitors (MAOI's)

Stop use

Stop use and ask a doctor if, nervousness, dizziness, or sleeplessness occur, sympton do not get better within 7 days or are accompanied by fever, cough lasts for more than 7 days, comes back, or is accompanied by fever, rash, or persistent headache. These can be signs of a serious condition.

Pregnancy or breast feeding, ask a health professional before use. Keep out of reach of children. In case of accidental overdose, get medical or professional help or contact a Poison Control Center immediatly.

Directions

Directions, do not exceed recommended dosage, do not take more than 6 doses in any 24 hours period, keep dosing cup for use with this product, ml=mililiters.

Adults and children 12 years & over 5 ml every 4 hours

children 6 to under 12 years age 2.5 ml every 4 hours

children 4 to 6 years of age 1.25 ml every 4 hours

children under 6 years of age Consult a doctor

other information

Store at room temperature , between 15-30 oC

Keep thigtly closed

Save carton for complete drug facts

Questions

Call 1-787-848-9114, Monday-Friday 9 AM --5PM EST

Call your doctor for medical advice in the event of side effects.

Keep out of reach of children section

In case of accidental overdose, get medical or professional help or contact a Poison Control Center immediatly.

Indication and usage section

Do not exceed recommended dosage, do not take more than 6 doses in any 24 hours period, keep dosing cup for use with this product, ml=mililiters.

Adults and children 12 years & over 5 ml every 4 hours

children 6 to under 12 years age 2.5 ml every 4 hours

children 4 to 6 years of age 1.25 ml every 4 hours

children under 6 years of age Consult a doctor

Principal panel

maximun strength

Giltuss Cold & cold

Alcohol free

Sugar free

Dye free

Cough, Phlem & Stuffy nose

Non-drowsy

Cherry flavor

4 flox 118 ml